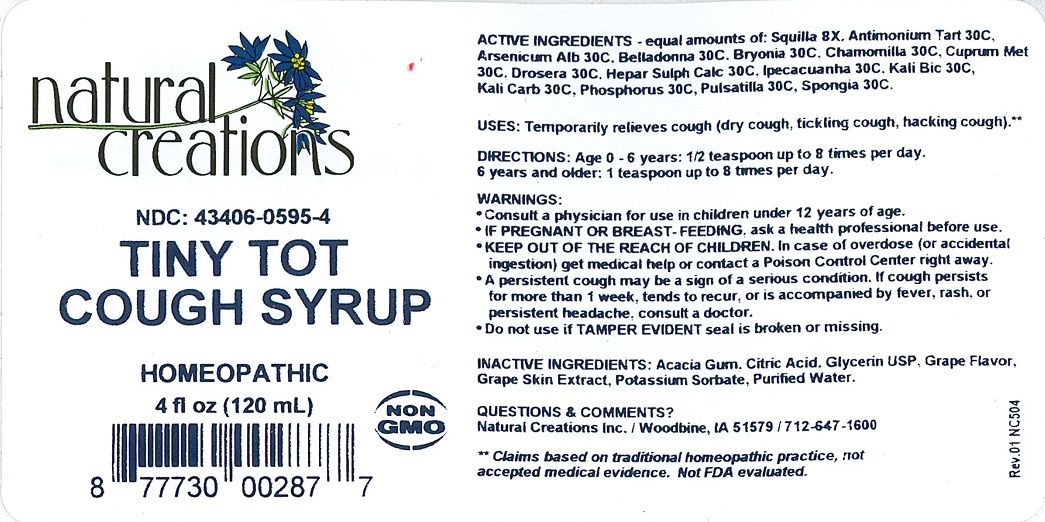 DRUG LABEL: Tiny Tot Cough Syrup
NDC: 43406-0595 | Form: SYRUP
Manufacturer: Natural Creations, Inc
Category: homeopathic | Type: HUMAN OTC DRUG LABEL
Date: 20251218

ACTIVE INGREDIENTS: DRIMIA MARITIMA BULB 8 [hp_X]/1 mL; ANTIMONY POTASSIUM TARTRATE 30 [hp_C]/1 mL; ARSENIC TRIOXIDE 30 [hp_C]/1 mL; ATROPA BELLADONNA 30 [hp_C]/1 mL; BRYONIA ALBA ROOT 30 [hp_C]/1 mL; MATRICARIA CHAMOMILLA WHOLE 30 [hp_C]/1 mL; copper 30 [hp_C]/1 mL; DROSERA ROTUNDIFOLIA WHOLE 30 [hp_C]/1 mL; CALCIUM SULFIDE 30 [hp_C]/1 mL; IPECAC 30 [hp_C]/1 mL; POTASSIUM DICHROMATE 30 [hp_C]/1 mL; POTASSIUM CARBONATE 30 [hp_C]/1 mL; PHOSPHORUS 30 [hp_C]/1 mL; PULSATILLA VULGARIS WHOLE 30 [hp_C]/1 mL; SPONGIA OFFICINALIS SKELETON, ROASTED 30 [hp_C]/1 mL
INACTIVE INGREDIENTS: ACACIA; CITRIC ACID MONOHYDRATE; GLYCERIN; VITIS VINIFERA ANTHOCYANINS; POTASSIUM SORBATE; WATER

Tiny Tot Cough Syrup

ACTIVE INGREDIENT

ACTIVE INGREDIENTS - equal amounts of: Squilla 8X, Antimonium Tart 30C, Arsenicum Alb 30C, Belladonna 30C, Bryonia 30C, Chamomilla 30C, Cuprum Met 30C, Drosera 30C, Hepar Sulph Calc 30C, Ipecacuanha 30C, Kali Bic 30C, Kali Carb 30C, Phosphorus 30C, Pulsatilla 30C, Spongia 30C

INDICATIONS AND USAGE

USES: Temporarily relieves cough (dry cough, tickling cough, hacking cough).**

PURPOSE

USES: Temporarily relieves cough (dry cough, tickling cough, hacking cough).**

DOSAGE AND ADMINISTRATION

DIRECTIONS: Age 0-6 years: 1/2 teaspoon up to 8 times per day. 6 years and older: 1 teaspoon up to 8 times per day.

KEEP OUT OF REACH OF CHILDREN

KEEP OUT OF THE REACH OF CHILDREN. In case of overdose (or accidental ingestion) get medical help or contact a Poison Control Center right away.

WARNINGS:

- Consult a physician for use in children under 12 years of age.
- IF PREGNANT OR BREAST-FEEDING, ask a health care professional before use.
- KEEP OUT OF THE REACH OF CHILDREN. In case of overdose (or accidental ingestion) get medical help or contact a Poison Control Center right away.
- A persistent cough may be a sign of a more serious condition. If cough persists for more than 1 week, tends to recur, or is accompanied be fever, rash, or persistent headache, consult a doctor.
- Do not use if TAMPER EVIDENT seal is broken or missing.

INACTIVE INGREDIENT

INACTIVE INGREDIENTS: Acacia Gum, Citric Acid, Glycerin USP, Grape Flavor, Grape Skin Extract, Potassium Sorbate, Purified Water

QUESTIONS & COMMENTS?

Natural Creations, Inc. / Woodbine, IA 51579 / 712-647-1600

REFERENCES

**Claims based on traditional homeopathic practice, not accepted medical evidence. Not FDA evaluated.

PACKAGE LABEL

NDC:43406-0595-4

Tiny Tot Cough Syrup

HOMEOPATHIC

4 fl oz (120mL)